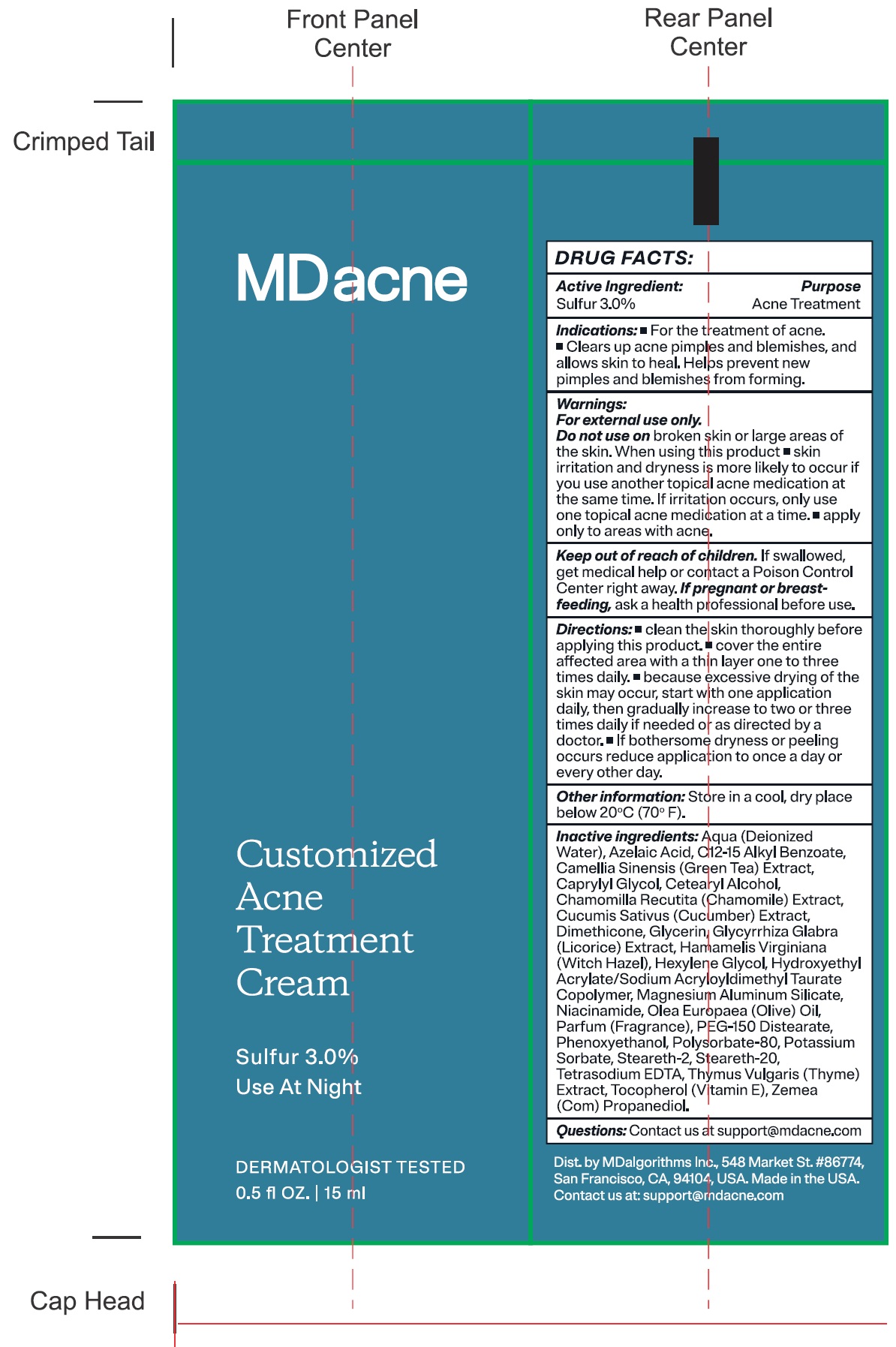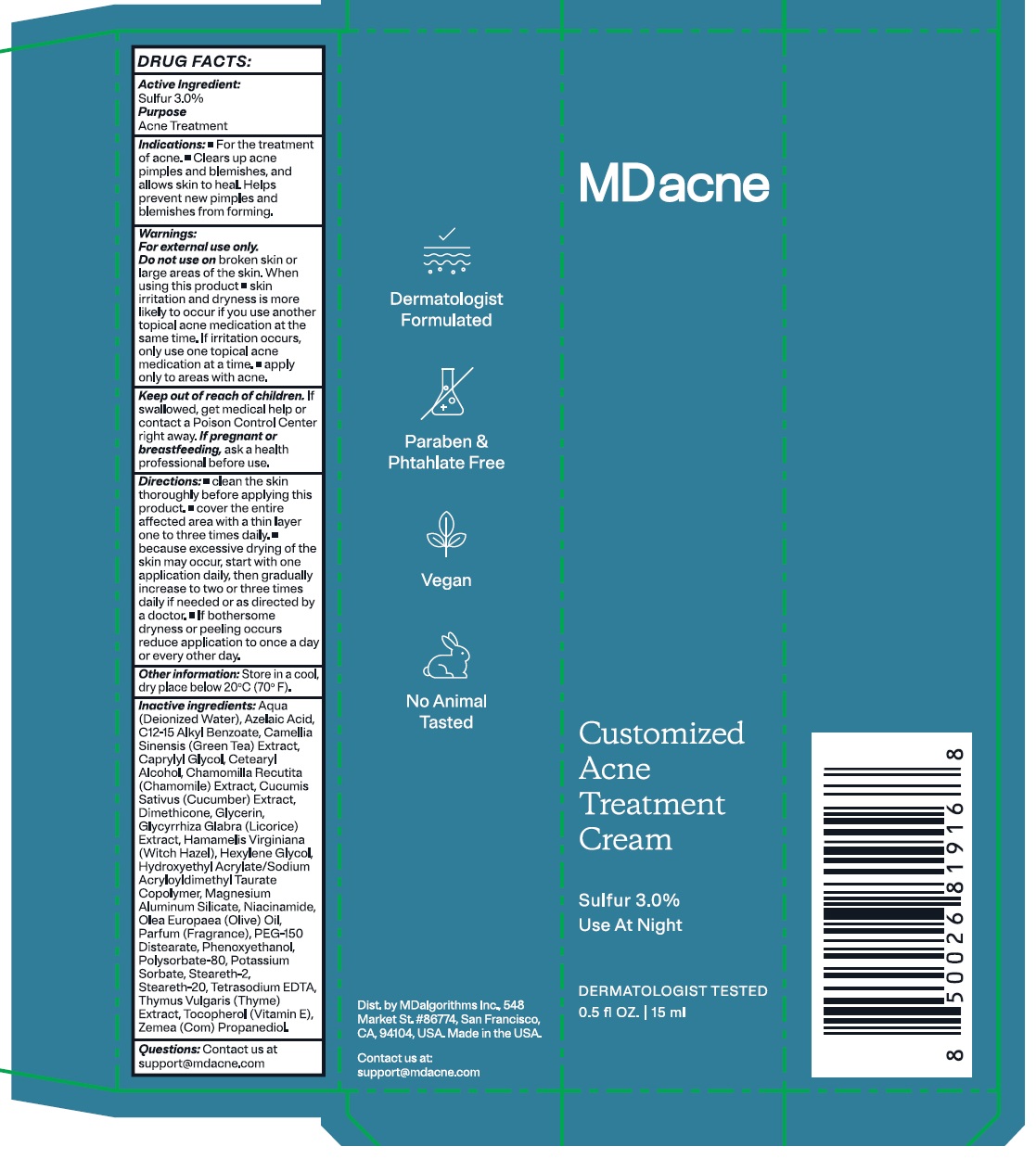 DRUG LABEL: MDacne Customized Acne Treatment Sulfur
NDC: 71804-535 | Form: CREAM
Manufacturer: MDAlgorithms Inc
Category: otc | Type: HUMAN OTC DRUG LABEL
Date: 20240926

ACTIVE INGREDIENTS: SULFUR 30 mg/1 mL
INACTIVE INGREDIENTS: WATER; AZELAIC ACID; ALKYL (C12-15) BENZOATE; GREEN TEA LEAF; CAPRYLYL GLYCOL; CETOSTEARYL ALCOHOL; CHAMOMILE; CUCUMBER; DIMETHICONE; GLYCERIN; GLYCYRRHIZA GLABRA; WITCH HAZEL; HEXYLENE GLYCOL; MAGNESIUM ALUMINUM SILICATE; NIACINAMIDE; GREEN OLIVE; PEG-150 DISTEARATE; PHENOXYETHANOL; POLYSORBATE 80; POTASSIUM SORBATE; STEARETH-2; STEARETH-20; EDETATE SODIUM; THYME; .ALPHA.-TOCOPHEROL ACETATE

MDacne Customized Acne Treatment Cream Sulfur 3.0%

Active Ingredient:

Sulfur 3.0%

Purpose

Acne Treatment

Indications:

- For the treatment of acne.
- Clears up acne pimples and blemishes, and allows skin to heal. Helps prevent new pimples and blemishes from forming.

Warnings:

For external use only.

Do not use on

broken skin or large areas of the skin.

When using this product

- skin irritation and dryness is more likely to occur if you use another topical medication at the same time. If irritation occurs, only use one topical acne medication at a time.
- apply only to areas with acne.

Keep out of reach of children.

If swallowed, get medical help or contact a Poison Control Center right away.

If pregnant or breastfeeding,

ask a health professional before use.

Directions:

- clean the skin thoroughly before applying this product.
- cover the entire affected area with a thin layer one to three times daily
- because excessive drying of the skin may occur, start with one application daily, then gradually increase to two or three times daily if needed or as directed by a doctor
- If bothersome dryness or peeling occurs, reduce application to once a day or every other day.

Other information:

Store in a cool, dry place below 20ºC (70ºF).

Inactive Ingredients:

Aqua (Deionized Water), Azelaic Acid, C12-15 Alkyl Benzoate, Camellia Sinensis (Green Tea) Extract, Caprylyl Glycol, Cetearyl Alcohol, Chamomilla Recutita (Chamomile) Extract, Cucumis Sativus (Cucumber) Fruit Extract, Dimethicone, Glycerin, Glycyrrhiza Glabra (Licorice Extract, Hamamelis Viginiana (Witch Hazel), Hexylene Glycol, Hydroxyethyl Acrylate/Sodium Acryloyldimethyl Taurate Copolymer, Magnesium Aluminum Silicate, Niacinamide, Olea Europaea (Olive) Oil, Parfum (Fragrance), PEG-150 Distearate, Phenoxyethanol, Polysorbate-80, Potassium Sorbate, Steareth-2, Steareth-20, Tetrasodium EDTA, Thymus Vulgaris (Thyme) Extract, Tocopheryl Acetate (Vitamin E), Zemea (Com) Propanediol.

Questions:

Contact us at support@mdacne.com